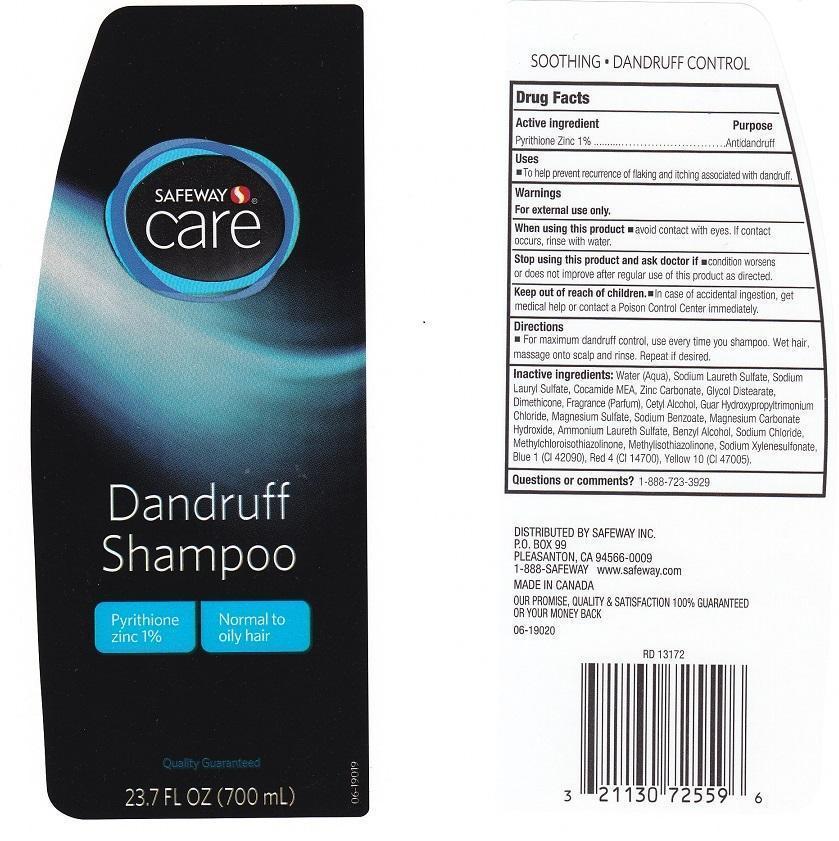 DRUG LABEL: SAFEWAY CARE
NDC: 21130-427 | Form: LIQUID
Manufacturer: SAFEWAY INC
Category: otc | Type: HUMAN OTC DRUG LABEL
Date: 20131217

ACTIVE INGREDIENTS: PYRITHIONE ZINC 10 mg/1 mL
INACTIVE INGREDIENTS: WATER; SODIUM LAURETH SULFATE; SODIUM LAURYL SULFATE; COCO MONOETHANOLAMIDE; ZINC CARBONATE; GLYCOL DISTEARATE; DIMETHICONE; CETYL ALCOHOL; GUAR HYDROXYPROPYLTRIMONIUM CHLORIDE (1.7 SUBSTITUENTS PER SACCHARIDE); MAGNESIUM SULFATE; SODIUM BENZOATE; MAGNESIUM CARBONATE HYDROXIDE; AMMONIUM LAURETH-3 SULFATE; BENZYL ALCOHOL; SODIUM CHLORIDE; METHYLCHLOROISOTHIAZOLINONE; METHYLISOTHIAZOLINONE; SODIUM XYLENESULFONATE; FD&C BLUE NO. 1; FD&C RED NO. 4; D&C YELLOW NO. 10

DRUG FACTS

ACTIVE INGREDIENT

PYRITHIONE ZINC 1%

PURPOSE

ANTIDANDRUFF

USES

TO HELP PREVENT RECURRENCE OF FLAKING AND ITCHING ASSOCIATED WITH DANDRUFF

WARNINGS

FOR EXTERNAL USE ONLY

WHEN USING THIS PRODUCT

AVOID CONTACT WITH EYES. IF CONTACT OCCURS, RINSE WITH WATER

STOP USING THIS PRODUCT AND ASK DOCTOR IF

CONDITION WORSENS OR DOES NOT IMPROVE AFTER REGULAR USE OF THIS PRODUCT AS DIRECTED

KEEP OUT OF REACH OF CHILDREN

IN CASE OF ACCIENTAL INGESTION, GET MEDICAL HELP OR CONTACT A POISON CONTROL CENTER IMMEDIATELY

DIRECTIONS

FOR MAXIMUM DANDRUFF CONTROL, USE EVERY TIME YOU SHAMPOO. WET HAIR, MASSAGE ONTO SCALP AND RINSE. REPEAT IF DESIRED

INACTIVE INGREDIENTS

WATER (AQUA), SODIUM LAURETH SULFATE, SODIUM LAURYL SULFATE, COCAMIDE MEA, ZINC CARBONATE, GLYCOL DISTEARATE, DIMETHICONE, FRAGRANCE (PARFUM), CETYL ALCOHOL, GUAR HYDROXPROPYLTRIMONIUM CHLORIDE, MAGNESIUM SULFATE, SODIUM BENZOATE, MAGNESIUM CARBONATE HYDROXIDE, AMMONIUM LAURETH SULFATE, BENZYL ALCOHOL, SODIUM CHLORIDE, METHYLCHLOROISOTHIAZOLINONE, METHYLISOTHIAZOLINONE, SODIUM XYLENESULFONATE, BLUE 1 (CI 42090), RED 4 (CI 14700), YELLOW 10 (CI 47005).

QUESTIONS OR COMMENTS?

1-888-723-3929